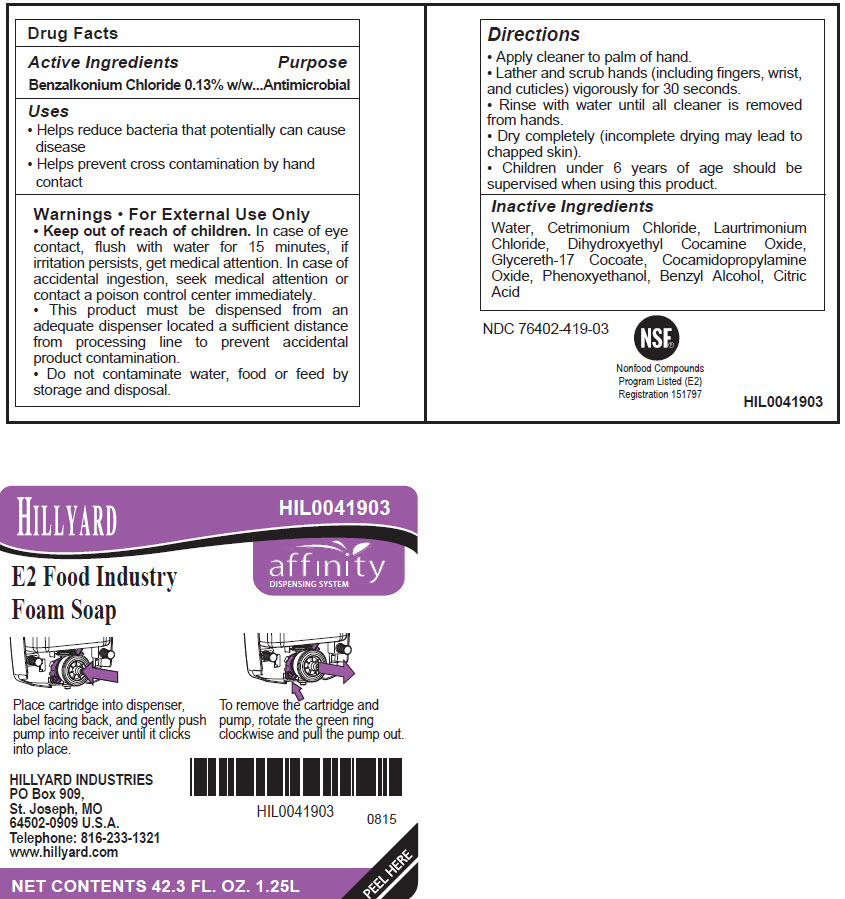 DRUG LABEL: Hillyard E2 Food Industry Foaming
NDC: 76402-419 | Form: LIQUID
Manufacturer: Hillyard GMP
Category: otc | Type: HUMAN OTC DRUG LABEL
Date: 20241230

ACTIVE INGREDIENTS: BENZALKONIUM CHLORIDE 0.13 g/100 mL
INACTIVE INGREDIENTS: WATER; CETRIMONIUM CHLORIDE; LAURTRIMONIUM CHLORIDE; DIHYDROXYETHYL COCAMINE OXIDE; GLYCERETH-17 COCOATE; COCAMIDOPROPYLAMINE OXIDE; PHENOXYETHANOL; BENZYL ALCOHOL; ANHYDROUS CITRIC ACID

Hillyard E2 Food Industry Foam Soap

Active ingredient

Benzalkonium Chloride 0.13% w/w

Purpose

Antimicrobial

Uses

- Helps reduce bacteria that potentially can cause disease
- Helps prevent cross contamination by hand contact

Warnings

- For External Use Only
- This product must be dispensed from an adequate dispenser located a sufficient distance from processing line to prevent accidental product contamination.
- Do not contaminate water, food or feed by storage and disposal.

Keep Out of Reach of Children

- In case of eye contact, flush with water for 15 minutes, if irritation persists, get medical attention. In case of accidental ingestion, seek medical attention or contact a poison control center immediately.

Directions

- Apply cleaner to palm of hand.
- Lather and scrub hands (including fingers, wrist, and cuticles) vigorously for 30 seconds.
- Rinse with water until all cleaner is removed from hands.
- Dry completely (incomplete drying may lead to chapped skin).
- Children under 6 years of age should be supervised when using this product.

Inactive Ingredients

Water, Cetrimonium Chloride, Laurtrimonium Chloride, Dihydroxyethyl Cocamine Oxide, Glycereth-17 Cocoate, Cocamidopropylamine Oxide, Phenoxyethanol, Benzyl Alcohol, Citric Acid

Package/Label Principal Display Panel

Hillyard
E2 Food Industry
Foam Soap

HIL0041903

affinity
DISPENSING SYSTEM

Place cartridge into dispenser, label facing back, and gently push pump into receiver until it clicks into place.

To remove the cartridge and pump, rotate the green ring clockwise and pull the pump out.

HILLYARD INDUSTRIES
PO Box 909,
St. Joseph, MO
64502-0909 U.S.A.
Telephone: 816-233-1321
www.hillyard.com

NET CONTENTS 42.3 FL. OZ. 1.25L
PEEL HERE

Carton Label